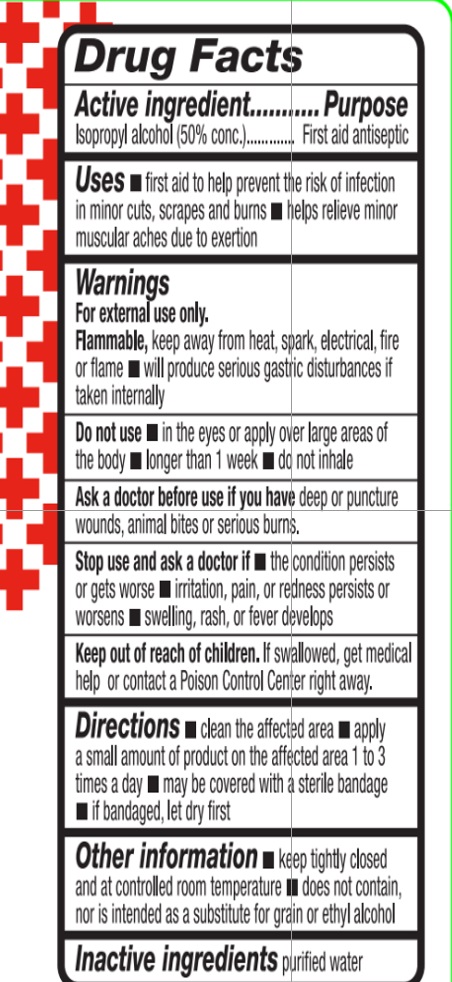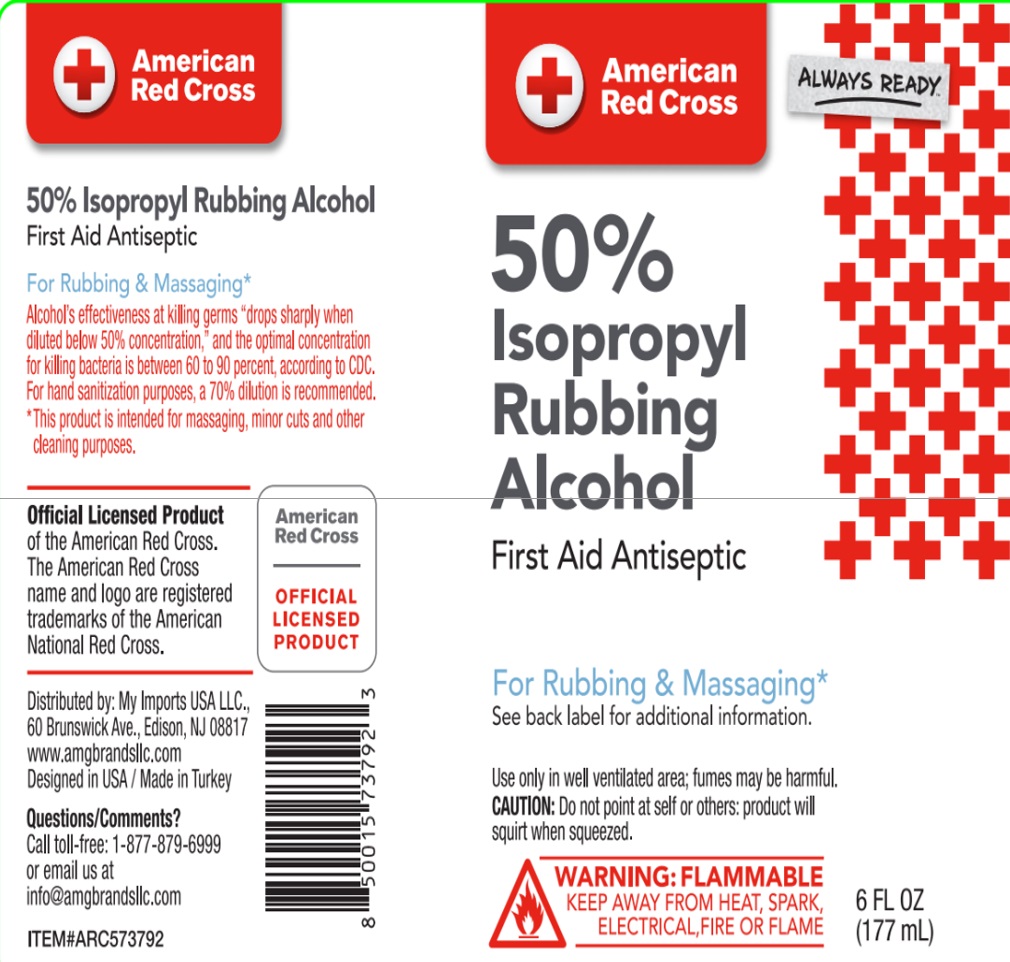 DRUG LABEL: American Red Cross 6oz, 50% Isopropyl Alcohol
NDC: 51628-3792 | Form: SPRAY
Manufacturer: MY IMPORTS USA LLC
Category: otc | Type: HUMAN OTC DRUG LABEL
Date: 20241213

ACTIVE INGREDIENTS: ISOPROPYL ALCOHOL 88.5 mL/177 mL
INACTIVE INGREDIENTS: AQUA 88.5 mL/177 mL

AMERICAN RED CROSS IPA 50%

ACTIVE INGREDIENT

Active ingredient .... Purpose

Isopropyl alcohol (50% conc).......First aid antiseptic

Ask a doctor before use if you have deep or puncture wounds, animal bites or serious burns

Do not use in the eyes or apply over large areas of the body

longer than 1 week

do not inhale

Keep out of reach of children. If swallowed, get medical help or contact a Poison Control Center right away.

STOP USE

Stop use and ask a doctor if the condition persists or gets worse

irritation, pain or redness persists or worsens

swelling, rash, or fever develops

OTHER INFORMATION

Other information? keep tightly closed and at controlled room temperature

does not contain, nor is intended as a substitute for grain or ethyl alcohol

WARNINGS

For external use only

Flammable, keep away from hear, spark, electrical, fire or flame

will produce serious gastric disturbances if taken internally

DIRECTIONS

clean the affected area

apply a small amount of product on the affected area 1 to 3 times a day

may be covered with a sterile bandage

if bandaged, let dry first

INACTIVE INGREDIENT

Inactive ingredients: purified water

DIRECTIONS

Directions: clean the affected area

apply a small amount of product on the affected area 1 to 3 times a day

may be covered with a sterile bandage

if bandaged, let dry first

USES

First aid to help prevent the risk of infection in minor cuts, scrapes and burns

helps relieve minor muscular aches due to extertion